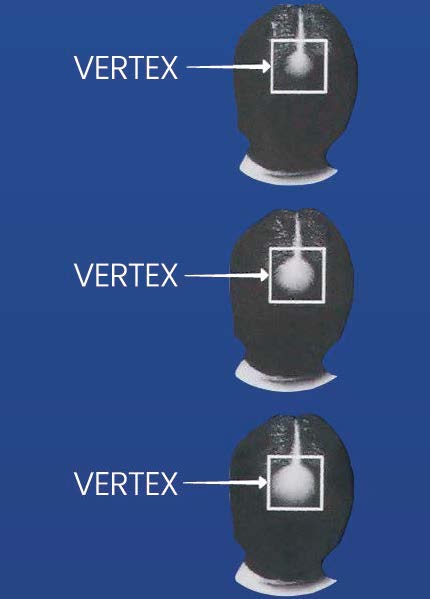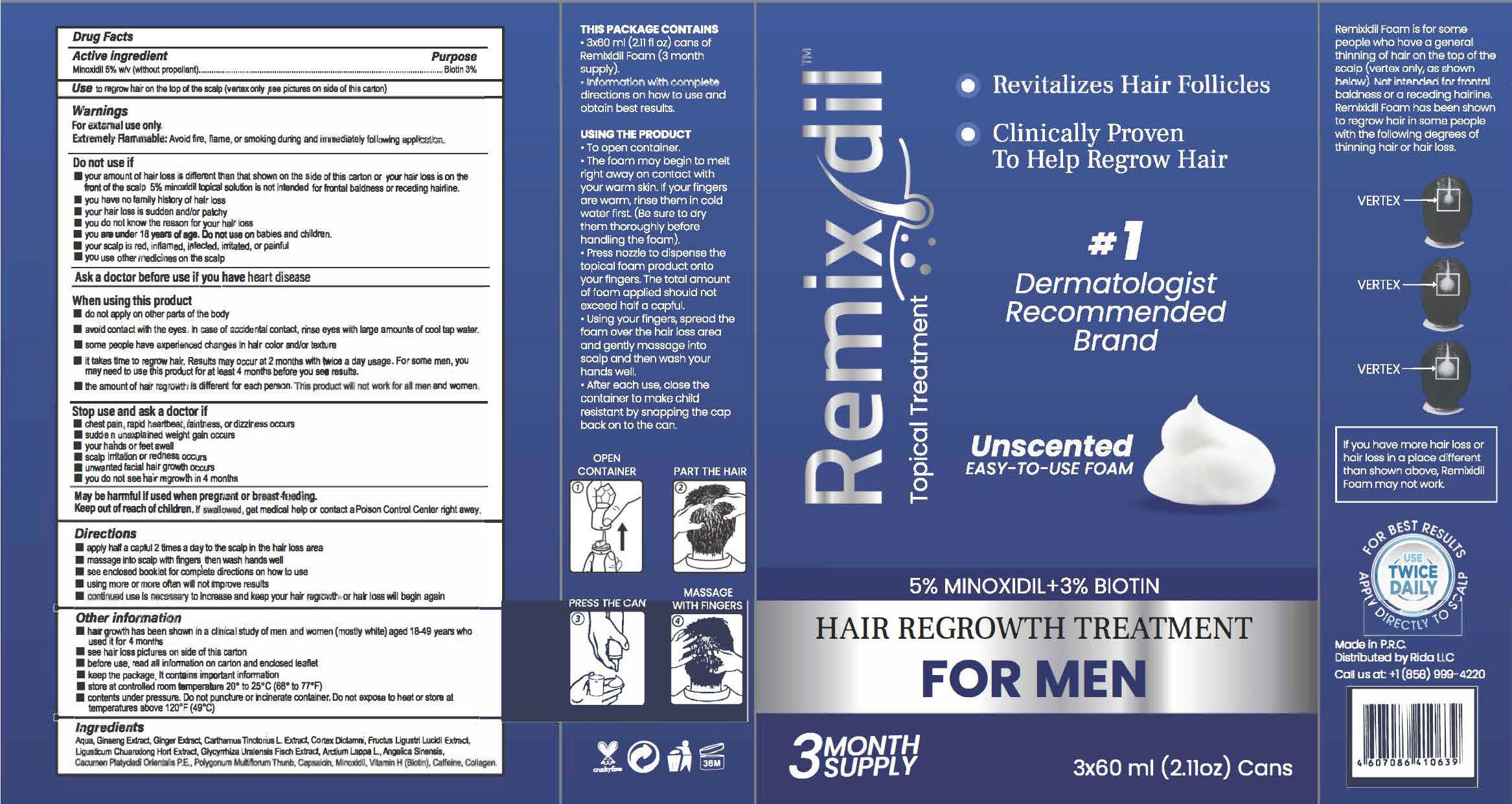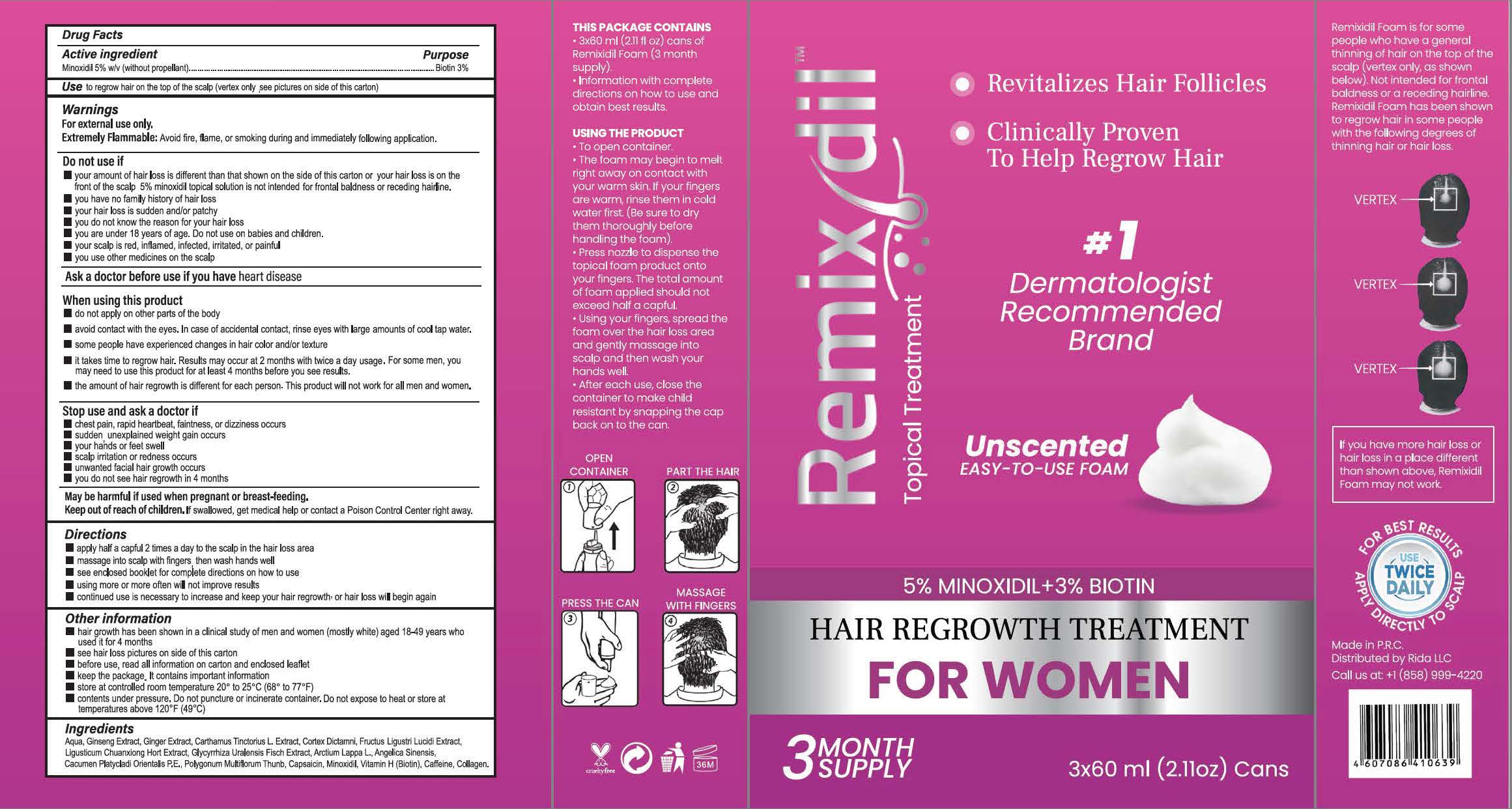 DRUG LABEL: Hair regrowth treatment
NDC: 81653-005 | Form: LIQUID
Manufacturer: Guangzhou Jianyuan Biological Technology.Co.,Ltd
Category: otc | Type: HUMAN OTC DRUG LABEL
Date: 20250116

ACTIVE INGREDIENTS: MINOXIDIL 5 g/100 mL
INACTIVE INGREDIENTS: ALCOHOL; LIGUSTICUM SINENSE SUBSP. CHUANXIONG ROOT; CAPSAICIN; DICTAMNUS DASYCARPUS ROOT; PLATYCLADUS ORIENTALIS WHOLE; LIGUSTRUM LUCIDUM FRUIT; GLYCYRRHIZA URALENSIS WHOLE; REYNOUTRIA MULTIFLORA ROOT; ANGELICA SINENSIS WHOLE; BIOTIN; WATER; CARTHAMUS TINCTORIUS WHOLE; ASIAN GINSENG

81653-005 Update

ACTIVE INGREDIENT

Minoxidil 5% w/v

PURPOSE

Use to regrow hair on the top of the scalp (vertex only)

INDICATIONS AND USAGE

Remixidil Foam is for some people who have a general thinning of hair on the top of the scalp (vertex only, as shownbelow). Not intended for frontal baldness or a receding hairline. Remixidil Foam has been shown to regrow hair in some people with the following degrees of thinning hair or hair loss.

WARNINGS

For external use only.
Extremely Flammable: Avoid fire, flame, or smoking during and immediately following application.

May be harmful if used when pregnant or breast-feeding.

Stop use and ask a doctor if
chest pain, rapid heartbeat, faintness, or dizziness occurs
sudden unexplained weight gain occurs
your hands or feet swell
scalp irritation or redness occursunwanted facial hair growth occurs
you do not see hair regrowth in 4 months

Ask a doctor before use if you have heart disease

When using this product
do not apply on other parts of the body
avoid contact with the eyes. In case of accidental contact, rinse eyes with large amounts of cool tap water.
some people have experienced changes in hair color and/or texture

it takes time to regrow hair. Results may occur at 2 months with twice a day usage.For some men, youmay need to use this product for at least 4 months before you see results.
the amount of hair regrowth is different for each person. This product will not work for all men and women

Keep out of reach of children.lf swallowed, get medical help or contact a Poison Control Center right away.

DOSAGE AND ADMINISTRATION

apply half a capful 2 times a day to the scalp in the hair loss area
massage into scalp with fingers then wash hands well
see enclosed booklet for complete directions on how to use
using more or more often will not improve results
continued use is necessary to increase and keep your hair regrowth or hair loss will begin again

STORAGE AND HANDLING

store at controlled room temperature 20° to 25C (68° to 77°F)
contents under pressure. Do not puncture or incinerate container. Do not expose to heat or store attemperatures above 120°F(49°c)
lngredients

OTHER SAFETY INFORMATION

before use, read all information on carton and enclosed leafletkeep the package, It contains important information

lnactive ingredients

Water, Polygonum multiflorum Thunb, Angelica Sinensis, Vitamin H.(Biotin), Cacumen Platycladi Orientalis, Ginseng Extract, Carthamus tinctorius L. Extract, Cortex Dictamni , Fructus Ligustri Lucidi Extract , Alcohol, Ligusticum Chuanxiong Hort Extract, Glycyrrhiza uralensis Fisch Extract, Capsaicin